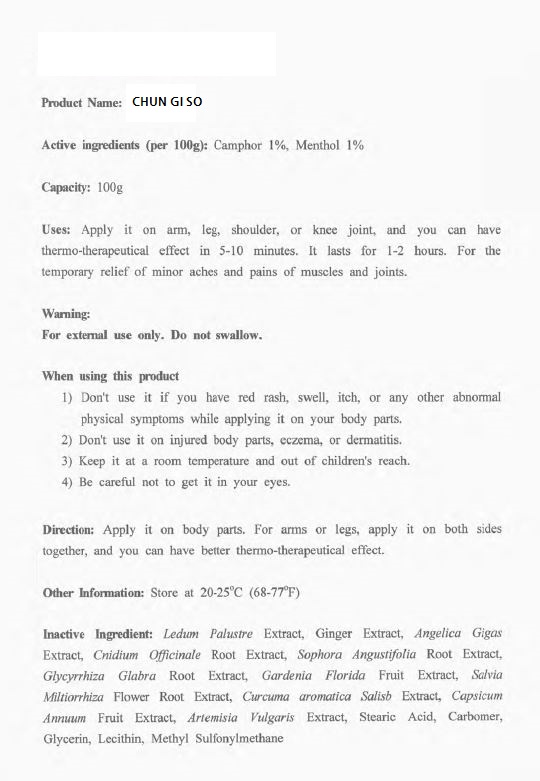 DRUG LABEL: Chun Gi So
NDC: 73426-0001 | Form: CREAM
Manufacturer: CHO WELL GF
Category: otc | Type: HUMAN OTC DRUG LABEL
Date: 20191117

ACTIVE INGREDIENTS: MENTHOL 1 g/100 g; CAMPHOR (NATURAL) 1 g/100 g
INACTIVE INGREDIENTS: ANGELICA GIGAS ROOT OIL

Drug Facts

ACTIVE INGREDIENT

camphor, menthol

INACTIVE INGREDIENT

ledum palustre extract, ginger extract, angelica gigas extract, etc

PURPOSE

temporary relief of minor aches and pains of muscles and joints

keep out of reach of the children

INDICATIONS AND USAGE

apply it on body parts, for arms or legs, apply it on both sides together, and you can have better thermo-therapeutical effect

do not use if you have red rash, swell, itch, or any other abnormal physical symptoms while applying it on your body parts

do not use it on injured body parts, eczema, or dermatitis

keep it at a room temperature and out of children's reach

be careful not to get it in your eyes

DOSAGE AND ADMINISTRATION

for external use only